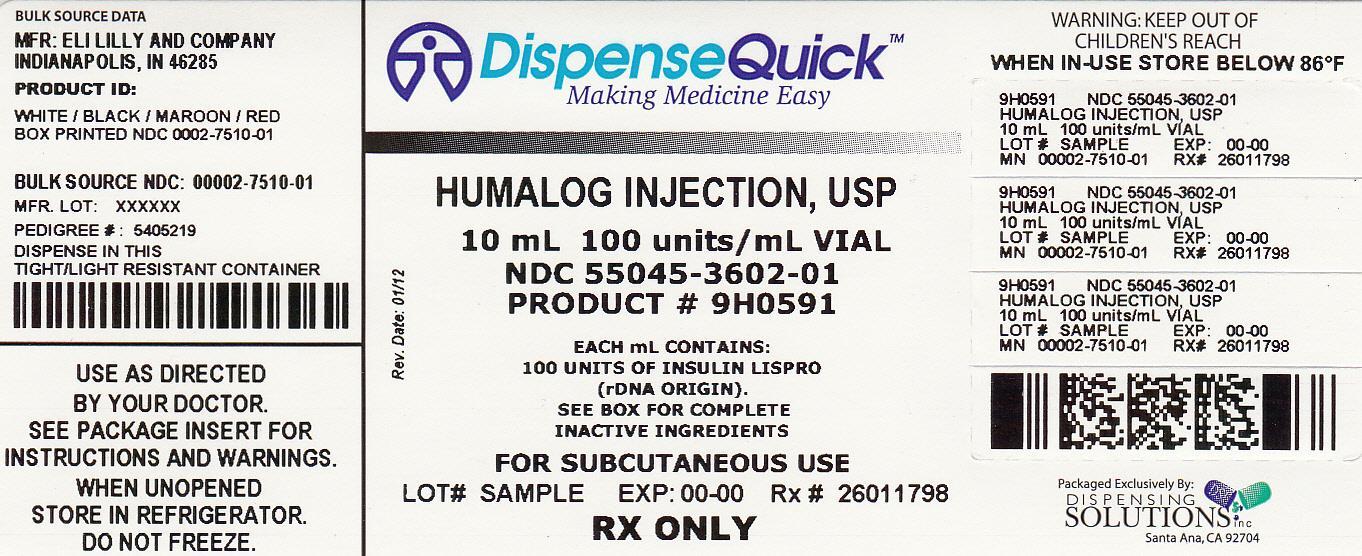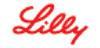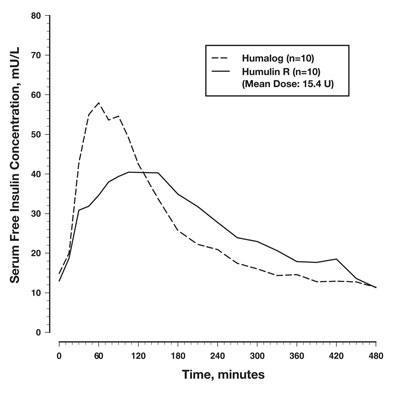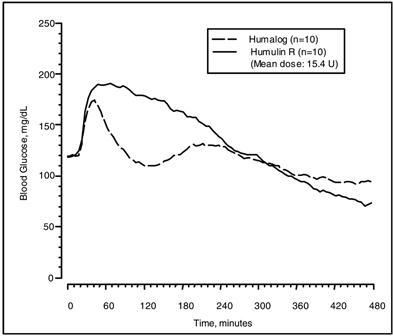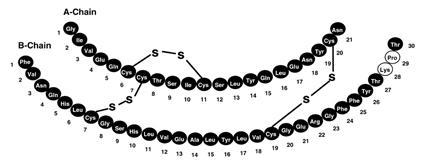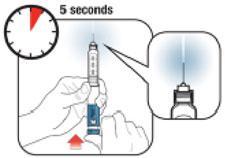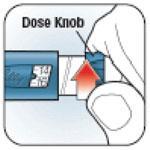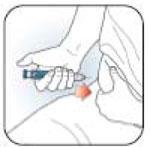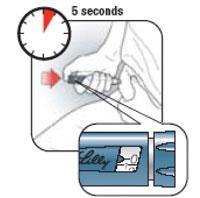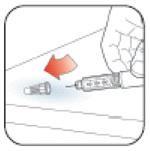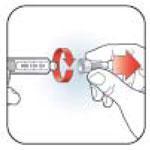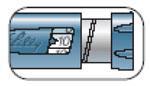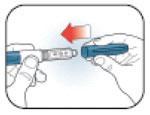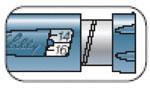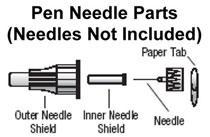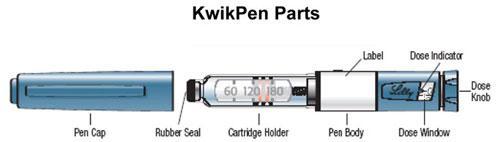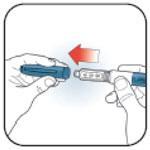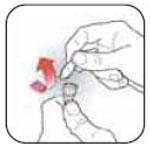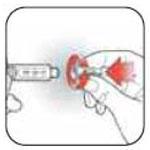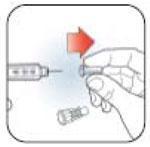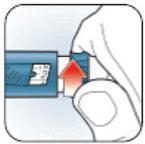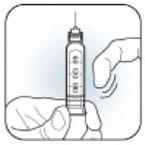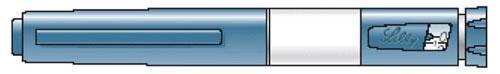 DRUG LABEL: Humalog
NDC: 55045-3602 | Form: INJECTION, SOLUTION
Manufacturer: Dispensing Solutions, Inc.
Category: prescription | Type: HUMAN PRESCRIPTION DRUG LABEL
Date: 20120927

ACTIVE INGREDIENTS: Insulin lispro 100 [iU]/1 mL
INACTIVE INGREDIENTS: Glycerin 16 mg/1 mL; Sodium Phosphate, Dibasic 1.88 mg/1 mL; Metacresol 3.15 mg/1 mL; Zinc .0197 mg/1 mL; Phenol; Water; Hydrochloric acid; Sodium hydroxide

HIGHLIGHTS OF PRESCRIBING INFORMATION

These highlights do not include all the information needed to use HUMALOG safely and effectively. See full prescribing information for HUMALOG.
Humalog (insulin lispro injection, USP [rDNA origin]) for injection
Initial U.S. Approval: 1996

RECENT MAJOR CHANGES

Dosage and Administration, Continuous Subcutaneous Infusion (Insulin Pump) (2.3) | 05/2011
Warnings and Precautions, Subcutaneous Insulin Infusion Pumps (5.7) | 05/2011

1 INDICATIONS AND USAGE

HUMALOG® is a rapid acting human insulin analog indicated to improve glycemic control in adults and children with diabetes mellitus. (1)

2 DOSAGE AND ADMINISTRATION

The dosage of HUMALOG must be individualized. (2.1)

Subcutaneous Injection | Administer within 15 minutes before a meal or immediately after a meal. Use in a regimen with an intermediate- or long-acting insulin. (2.2)
Continuous Subcutaneous Infusion Pump | Change the HUMALOG in the reservoir at least every 7 days, change the infusion set, and the infusion set insertion site at least every 3 days. HUMALOG must not be mixed or diluted when used in an external insulin infusion pump. (2.3)

3 DOSAGE FORMS AND STRENGTHS

HUMALOG 100 units/mL (U-100) is available as: (3)

- 10 mL vials
- 3 mL vials
- 3 mL prefilled pens
- 3 mL Humalog® KwikPen™ (prefilled)
- 3 mL cartridges

4 CONTRAINDICATIONS

- Do not use during episodes of hypoglycemia. (4)
- Do not use in patients with hypersensitivity to HUMALOG or any of its excipients. (4)

5 WARNINGS AND PRECAUTIONS

- Dose adjustment and monitoring: Closely monitor blood glucose in all patients treated with insulin. Change insulin regimens cautiously and only under medical supervision. (5.1)
- Hypoglycemia: Most common adverse reaction of insulin therapy and may be life-threatening. (5.2)
- Allergic reactions: Severe, life-threatening, generalized allergy, including anaphylaxis, can occur with any insulin, including HUMALOG. (5.3)
- Hypokalemia: All insulins, including HUMALOG can cause hypokalemia, which if untreated, may result in respiratory paralysis, ventricular arrhythmia, and death. (5.4)
- Renal or hepatic impairment: Like all insulins, may require a reduction in the HUMALOG dose. (5.5)
- Mixing: HUMALOG for subcutaneous injection should not be mixed with insulins other than NPH insulin. Do not mix HUMALOG with any insulin for use in a continuous infusion pump. (5.6)
- Pump use: Select a new infusion site at least every 3 days and replace the HUMALOG in the pump reservoir at least every 7 days. (5.7)

6 ADVERSE REACTIONS

Adverse reactions associated with HUMALOG include hypoglycemia, allergic reactions, injection site reactions, lipodystrophy, pruritus, and rash. (6.1)

To report SUSPECTED ADVERSE REACTIONS, contact Eli Lilly and Company at 1-800-LillyRx (1-800-545-5979) or FDA at 1-800-FDA-1088 or www.fda.gov/medwatch.

7 DRUG INTERACTIONS

- Certain drugs may affect glucose metabolism and may necessitate insulin dose adjustment. (7)
- The signs of hypoglycemia may be reduced or absent in patients taking anti-adrenergic drugs (e.g., beta-blockers, clonidine, guanethidine, and reserpine). (7)

8 USE IN SPECIFIC POPULATIONS

Pediatrics: Has not been studied in children with type 2 diabetes. Has not been studied in children with type 1 diabetes <3 years of age. (8.4)

FULL PRESCRIBING INFORMATION

1 INDICATIONS AND USAGE

HUMALOG is an insulin analog indicated to improve glycemic control in adults and children with diabetes mellitus.

2 DOSAGE AND ADMINISTRATION

2.1 Dosage Considerations

When given subcutaneously, HUMALOG has a more rapid onset of action and a shorter duration of action than regular human insulin.

The dosage of HUMALOG must be individualized. Blood glucose monitoring is essential in all patients receiving insulin therapy.

The total daily insulin requirement may vary and is usually between 0.5 to 1 unit/kg/day. Insulin requirements may be altered during stress, major illness, or with changes in exercise, meal patterns, or coadministered drugs.

2.2 Subcutaneous Administration

HUMALOG should be given within 15 minutes before a meal or immediately after a meal.

HUMALOG given by subcutaneous injection should generally be used in regimens with an intermediate- or long-acting insulin.

HUMALOG administered by subcutaneous injection should be given in the abdominal wall, thigh, upper arm, or buttocks. Injection sites should be rotated within the same region (abdomen, thigh, upper arm, or buttocks) from one injection to the next to reduce the risk of lipodystrophy [see Adverse Reactions (6.1)].

2.3 Continuous Subcutaneous Infusion (Insulin Pump)

HUMALOG may be administered by continuous subcutaneous infusion by an external insulin pump. Do not use diluted or mixed insulins in external insulin pumps. Infusion sites should be rotated within the same region to reduce the risk of lipodystrophy [see Adverse Reactions (6.1)]. Change the HUMALOG in the reservoir at least every 7 days, change the infusion sets and the infusion set insertion site at least every 3 days.

The initial programming of the external insulin infusion pump should be based on the total daily insulin dose of the previous regimen. Although there is significant variability among patients, approximately 50% of the total dose is usually given as meal-related boluses of HUMALOG and the remainder is given as a basal infusion. HUMALOG is recommended for use in pump systems suitable for insulin infusion such as MiniMed, Disetronic, and other equivalent pumps [see For Patients Using Continuous Subcutaneous Insulin Pumps (17.2)].

3 DOSAGE FORMS AND STRENGTHS

HUMALOG 100 units per mL (U-100) is available as:

- 10 mL vials
- 3 mL vials
- 3 mL prefilled pens
- 3 mL Humalog KwikPen (prefilled)
- 3 mL cartridges

4 CONTRAINDICATIONS

HUMALOG is contraindicated:

- during episodes of hypoglycemia
- in patients who are hypersensitive to HUMALOG or to any of its excipients.

5 WARNINGS AND PRECAUTIONS

5.1 Dose Adjustment and Monitoring

Glucose monitoring is essential for patients receiving insulin therapy. Changes to an insulin regimen should be made cautiously and only under medical supervision. Changes in insulin strength, manufacturer, type, or method of administration may result in the need for a change in insulin dose. Concomitant oral antidiabetic treatment may need to be adjusted.

As with all insulin preparations, the time course of action for HUMALOG may vary in different individuals or at different times in the same individual and is dependent on many conditions, including the site of injection, local blood supply, or local temperature. Patients who change their level of physical activity or meal plan may require adjustment of insulin dosages.

5.2 Hypoglycemia

Hypoglycemia is the most common adverse effect associated with insulins, including HUMALOG. The risk of hypoglycemia increases with tighter glycemic control. Patients must be educated to recognize and manage hypoglycemia. Hypoglycemia can happen suddenly and symptoms may be different for each person and may change from time to time. Severe hypoglycemia can cause seizures and may be life-threatening or cause death.

The timing of hypoglycemia usually reflects the time-action profile of the administered insulin formulations. Other factors such as changes in food intake (e.g., amount of food or timing of meals), injection site, exercise, and concomitant medications may also alter the risk of hypoglycemia [see Drug Interactions (7)].

As with all insulins, use caution in patients with hypoglycemia unawareness and in patients who may be predisposed to hypoglycemia (e.g., the pediatric population and patients who fast or have erratic food intake). The patient's ability to concentrate and react may be impaired as a result of hypoglycemia. This may present a risk in situations where these abilities are especially important, such as driving or operating other machinery.

Rapid changes in serum glucose levels may induce symptoms similar to hypoglycemia in persons with diabetes, regardless of the glucose value. Early warning symptoms of hypoglycemia may be different or less pronounced under certain conditions, such as longstanding diabetes, diabetic nerve disease, use of medications such as beta-blockers [see Drug Interactions (7)], or intensified diabetes control. These situations may result in severe hypoglycemia (and, possibly, loss of consciousness) prior to the patient's awareness of hypoglycemia.

5.3 Hypersensitivity and Allergic Reactions

Severe, life-threatening, generalized allergy, including anaphylaxis, can occur with insulin products, including HUMALOG [see Adverse Reactions (6.1)].

5.4 Hypokalemia

All insulin products, including HUMALOG, cause a shift in potassium from the extracellular to intracellular space, possibly leading to hypokalemia. Untreated hypokalemia may cause respiratory paralysis, ventricular arrhythmia, and death. Use caution in patients who may be at risk for hypokalemia (e.g., patients using potassium-lowering medications, patients taking medications sensitive to serum potassium concentrations).

5.5 Renal or Hepatic Impairment

Frequent glucose monitoring and insulin dose reduction may be required in patients with renal or hepatic impairment [see Clinical Pharmacology (12.3)].

5.6 Mixing of Insulins

HUMALOG for subcutaneous injection should not be mixed with insulin preparations other than NPH insulin. If HUMALOG is mixed with NPH insulin, HUMALOG should be drawn into the syringe first. Injection should occur immediately after mixing.

Do not mix HUMALOG with other insulins for use in an external subcutaneous infusion pump.

5.7 Subcutaneous Insulin Infusion Pumps

When used in an external insulin pump for subcutaneous infusion, HUMALOG should not be diluted or mixed with any other insulin. Change the HUMALOG in the reservoir at least every 7 days, change the infusion sets and the infusion set insertion site at least every 3 days. HUMALOG should not be exposed to temperatures greater than 98.6°F (37°C).

Malfunction of the insulin pump or infusion set or insulin degradation can rapidly lead to hyperglycemia and ketosis. Prompt identification and correction of the cause of hyperglycemia or ketosis is necessary. Interim subcutaneous injections with HUMALOG may be required. Patients using continuous subcutaneous insulin infusion pump therapy must be trained to administer insulin by injection and have alternate insulin therapy available in case of pump failure [see Dosage and Administration (2.3), How Supplied/Storage and Handling (16), and Patient Counseling Information (17.2)].

5.8 Drug Interactions

Some medications may alter insulin requirements and the risk for hypoglycemia or hyperglycemia [see Drug Interactions (7)].

6 ADVERSE REACTIONS

The following adverse reactions are discussed elsewhere:

- Hypoglycemia [see Warnings and Precautions (5.2)].
- Hypokalemia [see Warnings and Precautions (5.4)].

6.1 Clinical Trial Experience

Because clinical trials are conducted under widely varying designs, the adverse reaction rates reported in one clinical trial may not be easily compared with those rates reported in another clinical trial, and may not reflect the rates actually observed in clinical practice.

The frequencies of Treatment-Emergent Adverse Events during HUMALOG clinical trials in patients with type 1 diabetes mellitus and type 2 diabetes mellitus are listed in the tables below.

Table 1: Treatment-Emergent Adverse Events in Patients with Type 1 Diabetes Mellitus (adverse events with frequency ≥5%)
Events, n (%) | Lispro (n=81) | Regular human insulin (n=86) | Total (n=167)
Flu syndrome | 28 (34.6) | 28 (32.6) | 56 (33.5)
Pharyngitis | 27 (33.3) | 29 (33.7) | 56 (33.5)
Rhinitis | 20 (24.7) | 25 (29.1) | 45 (26.9)
Headache | 24 (29.6) | 19 (22.1) | 43 (25.7)
Pain | 16 (19.8) | 14 (16.3) | 30 (18.0)
Cough increased | 14 (17.3) | 15 (17.4) | 29 (17.4)
Infection | 11 (13.6) | 18 (20.9) | 29 (17.4)
Nausea | 5 (6.2) | 13 (15.1) | 18 (10.8)
Accidental injury | 7 (8.6) | 10 (11.6) | 17 (10.2)
Surgical procedure | 5 (6.2) | 12 (14.0) | 17 (10.2)
Fever | 5 (6.2) | 10 (11.6) | 15 (9.0)
Abdominal pain | 6 (7.4) | 7 (8.1) | 13 (7.8)
Asthenia | 6 (7.4) | 7 (8.1) | 13 (7.8)
Bronchitis | 6 (7.4) | 6 (7.0) | 12 (7.2)
Diarrhea | 7 (8.6) | 5 (5.8) | 12 (7.2)
Dysmenorrhea | 5 (6.2) | 6 (7.0) | 11 (6.6)
Myalgia | 6 (7.4) | 5 (5.8) | 11 (6.6)
Urinary tract infection | 5 (6.2) | 4 (4.7) | 9 (5.4)

Table 2: Treatment-Emergent Adverse Events in Patients with Type 2 Diabetes Mellitus (adverse events with frequency ≥5%)
Events, n (%) | Lispro (n=714) | Regular human insulin (n=709) | Total (n=1423)
Headache | 63 (11.6) | 66 (9.3) | 149 (10.5)
Pain | 77 (10.8) | 71 (10.0) | 148 (10.4)
Infection | 72 (10.1) | 54 (7.6) | 126 (8.9)
Pharyngitis | 47 (6.6) | 58 (8.2) | 105 (7.4)
Rhinitis | 58 (8.1) | 47 (6.6) | 105 (7.4)
Flu syndrome | 44 (6.2) | 58 (8.2) | 102 (7.2)
Surgical procedure | 53 (7.4) | 48 (6.8) | 101 (7.1)

Insulin initiation and intensification of glucose control

Intensification or rapid improvement in glucose control has been associated with a transitory, reversible ophthalmologic refraction disorder, worsening of diabetic retinopathy, and acute painful peripheral neuropathy. However, long-term glycemic control decreases the risk of diabetic retinopathy and neuropathy.

Lipodystrophy

Long-term use of insulin, including HUMALOG, can cause lipodystrophy at the site of repeated insulin injections or infusion. Lipodystrophy includes lipohypertrophy (thickening of adipose tissue) and lipoatrophy (thinning of adipose tissue), and may affect insulin absorption. Rotate insulin injection or infusion sites within the same region to reduce the risk of lipodystrophy [see Dosage and Administration (2.2, 2.3)].

Weight gain

Weight gain can occur with insulin therapy, including HUMALOG, and has been attributed to the anabolic effects of insulin and the decrease in glucosuria.

Peripheral Edema

Insulin, including HUMALOG, may cause sodium retention and edema, particularly if previously poor metabolic control is improved by intensified insulin therapy.

Adverse Reactions with Continuous Subcutaneous Insulin Infusion (CSII)

In a 12-week, randomized, crossover study in adult patients with type 1 diabetes (n=39), the rates of catheter occlusions and infusion site reactions were similar for HUMALOG and regular human insulin treated patients (see Table 3).

Table 3: Catheter Occlusions and Infusion Site Reactions
 | HUMALOG (n=38) | Regular human insulin (n=39)
Catheter occlusions/month | 0.09 | 0.10
Infusion site reactions | 2.6% (1/38) | 2.6% (1/39)

In a randomized, 16-week, open-label, parallel design study of children and adolescents with type 1 diabetes, adverse event reports related to infusion-site reactions were similar for insulin lispro and insulin aspart (21% of 100 patients versus 17% of 198 patients, respectively). In both groups, the most frequently reported infusion site adverse events were infusion site erythema and infusion site reaction.

Allergic Reactions

Local Allergy — As with any insulin therapy, patients taking HUMALOG may experience redness, swelling, or itching at the site of the injection. These minor reactions usually resolve in a few days to a few weeks, but in some occasions, may require discontinuation of HUMALOG. In some instances, these reactions may be related to factors other than insulin, such as irritants in a skin cleansing agent or poor injection technique.

Systemic Allergy — Severe, life-threatening, generalized allergy, including anaphylaxis, may occur with any insulin, including HUMALOG. Generalized allergy to insulin may cause whole body rash (including pruritus), dyspnea, wheezing, hypotension, tachycardia, or diaphoresis.

In controlled clinical trials, pruritus (with or without rash) was seen in 17 patients receiving regular human insulin (n=2969) and 30 patients receiving HUMALOG (n=2944).

Localized reactions and generalized myalgias have been reported with injected metacresol, which is an excipient in HUMALOG [see Contraindications (4)].

Antibody Production

In large clinical trials with patients with type 1 (n=509) and type 2 (n=262) diabetes mellitus, anti-insulin antibody (insulin lispro-specific antibodies, insulin-specific antibodies, cross-reactive antibodies) formation was evaluated in patients receiving both regular human insulin and HUMALOG (including patients previously treated with human insulin and naive patients). As expected, the largest increase in the antibody levels occurred in patients new to insulin therapy. The antibody levels peaked by 12 months and declined over the remaining years of the study These antibodies do not appear to cause deterioration in glycemic control or necessitate an increase in insulin dose. There was no statistically significant relationship between the change in the total daily insulin dose and the change in percent antibody binding for any of the antibody types.

6.2 Postmarketing Experience

The following additional adverse reactions have been identified during post-approval use of HUMALOG. Because these reactions are reported voluntarily from a population of uncertain size, it is not always possible to reliably estimate their frequency or establish a causal relationship to drug exposure.

Medication errors in which other insulins have been accidentally substituted for HUMALOG have been identified during postapproval use [see Patient Counseling Information (17)].

7 DRUG INTERACTIONS

A number of drugs affect glucose metabolism and may require insulin dose adjustment and particularly close monitoring.

Following are some of the examples:

- Drugs That May Increase the Blood-Glucose-Lowering Effect of HUMALOG and Susceptibility to Hypoglycemia: Oral antidiabetic agents, salicylates, sulfonamide antibiotics, monoamine oxidase inhibitors, fluoxetine, pramlintide, disopyramide, fibrates, propoxyphene, pentoxifylline, ACE inhibitors, angiotensin II receptor blocking agents, and somatostatin analogs (e.g., octreotide).
- Drugs That May Reduce the Blood-Glucose-Lowering Effect of HUMALOG: corticosteroids, isoniazid, niacin, estrogens, oral contraceptives, phenothiazines, danazol, diuretics, sympathomimetic agents (e.g., epinephrine, albuterol, terbutaline), somatropin, atypical antipsychotics, glucagon, protease inhibitors, and thyroid hormones.
- Drugs That May Increase or Reduce the Blood-Glucose-Lowering Effect of HUMALOG: beta-blockers, clonidine, lithium salts, and alcohol. Pentamidine may cause hypoglycemia, which may sometimes be followed by hyperglycemia.
- Drugs That May Reduce the Signs of Hypoglycemia: beta-blockers, clonidine, guanethidine, and reserpine.

8 USE IN SPECIFIC POPULATIONS

8.1 Pregnancy

Pregnancy Category B. All pregnancies have a background risk of birth defects, loss, or other adverse outcome regardless of drug exposure. This background risk is increased in pregnancies complicated by hyperglycemia and may be decreased with good metabolic control. It is essential for patients with diabetes or history of gestational diabetes to maintain good metabolic control before conception and throughout pregnancy. In patients with diabetes or gestational diabetes insulin requirements may decrease during the first trimester, generally increase during the second and third trimesters, and rapidly decline after delivery. Careful monitoring of glucose control is essential in these patients. Therefore, female patients should be advised to tell their physicians if they intend to become, or if they become pregnant while taking HUMALOG.

Although there are limited clinical studies of the use of HUMALOG in pregnancy, published studies with human insulins suggest that optimizing overall glycemic control, including postprandial control, before conception and during pregnancy improves fetal outcome.

In a combined fertility and embryo-fetal development study, female rats were given subcutaneous insulin lispro injections of 5 and 20 units/kg/day (0.8 and 3 times the human subcutaneous dose of 1 unit/kg/day, based on units/body surface area, respectively) from 2 weeks prior to cohabitation through Gestation Day 19. There were no adverse effects on female fertility, implantation, or fetal viability and morphology. However, fetal growth retardation was produced at the 20 units/kg/day-dose as indicated by decreased fetal weight and an increased incidence of fetal runts/litter.

In an embryo-fetal development study in pregnant rabbits, insulin lispro doses of 0.1, 0.25, and 0.75 unit/kg/day (0.03, 0.08, and 0.24 times the human subcutaneous dose of 1 unit/kg/day, based on units/body surface area, respectively) were injected subcutaneously on Gestation days 7 through 19. There were no adverse effects on fetal viability, weight, and morphology at any dose.

8.3 Nursing Mothers

It is unknown whether insulin lispro is excreted in human milk. Because many drugs are excreted in human milk, caution should be exercised when HUMALOG is administered to a nursing woman. Use of HUMALOG is compatible with breastfeeding, but women with diabetes who are lactating may require adjustments of their insulin doses.

8.4 Pediatric Use

HUMALOG is approved for use in children for subcutaneous daily injections and for subcutaneous continuous infusion by external insulin pump. HUMALOG has not been studied in pediatric patients younger than 3 years of age. HUMALOG has not been studied in pediatric patients with type 2 diabetes [see Clinical Studies (14)].

As in adults, the dosage of HUMALOG must be individualized in pediatric patients based on metabolic needs and results of frequent monitoring of blood glucose.

8.5 Geriatric Use

Of the total number of subjects (n=2834) in eight clinical studies of HUMALOG, twelve percent (n=338) were 65 years of age or over. The majority of these had type 2 diabetes. HbA1c values and hypoglycemia rates did not differ by age. Pharmacokinetic/pharmacodynamic studies to assess the effect of age on the onset of HUMALOG action have not been performed.

10 OVERDOSAGE

Excess insulin administration may cause hypoglycemia and hypokalemia. Mild episodes of hypoglycemia usually can be treated with oral glucose. Adjustments in drug dosage, meal patterns, or exercise may be needed. More severe episodes with coma, seizure, or neurologic impairment may be treated with intramuscular/subcutaneous glucagon or concentrated intravenous glucose. Sustained carbohydrate intake and observation may be necessary because hypoglycemia may recur after apparent clinical recovery. Hypokalemia must be corrected appropriately.

11 DESCRIPTION

HUMALOG® (insulin lispro injection, USP [rDNA origin]) is a rapid-acting human insulin analog used to lower blood glucose. Insulin lispro is produced by recombinant DNA technology utilizing a non-pathogenic laboratory strain of Escherichia coli. Insulin lispro differs from human insulin in that the amino acid proline at position B28 is replaced by lysine and the lysine in position B29 is replaced by proline. Chemically, it is Lys(B28), Pro(B29) human insulin analog and has the empirical formula C257H383N65O77S6 and a molecular weight of 5808, both identical to that of human insulin.

HUMALOG has the following primary structure:

HUMALOG is a sterile, aqueous, clear, and colorless solution. Each milliliter of HUMALOG contains insulin lispro 100 units, 16 mg glycerin, 1.88 mg dibasic sodium phosphate, 3.15 mg Metacresol, zinc oxide content adjusted to provide 0.0197 mg zinc ion, trace amounts of phenol, and Water for Injection. Insulin lispro has a pH of 7.0 to 7.8. The pH is adjusted by addition of aqueous solutions of hydrochloric acid 10% and/or sodium hydroxide 10%.

12 CLINICAL PHARMACOLOGY

12.1 Mechanism of Action

Regulation of glucose metabolism is the primary activity of insulins and insulin analogs, including insulin lispro. Insulins lower blood glucose by stimulating peripheral glucose uptake by skeletal muscle and fat, and by inhibiting hepatic glucose production. Insulins inhibit lipolysis and proteolysis, and enhance protein synthesis.

12.2 Pharmacodynamics

HUMALOG has been shown to be equipotent to human insulin on a molar basis. One unit of HUMALOG has the same glucose-lowering effect as one unit of regular human insulin. Studies in normal volunteers and patients with diabetes demonstrated that HUMALOG has a more rapid onset of action and a shorter duration of activity than regular human insulin when given subcutaneously.

The time course of action of insulin and insulin analogs, such as HUMALOG, may vary considerably in different individuals or within the same individual. The parameters of HUMALOG activity (time of onset, peak time, and duration) as designated in Figure 1 should be considered only as general guidelines. The rate of insulin absorption, and consequently the onset of activity are known to be affected by the site of injection, exercise, and other variables [see Warnings and Precautions (5.1)].

Figure 1: Blood Glucose Levels After Subcutaneous Injection of Regular Human Insulin or HUMALOG (0.2 unit/kg) Immediately Before a High Carbohydrate Meal in 10 Patients with Type 1 Diabetes.a

a Baseline insulin concentration was maintained by infusion of 0.2 mU/min/kg human insulin.

12.3 Pharmacokinetics

Absorption and Bioavailability — Studies in healthy volunteers and patients with diabetes demonstrated that HUMALOG is absorbed more quickly than regular human insulin. In healthy volunteers given subcutaneous doses of HUMALOG ranging from 0.1 to 0.4 unit/kg, peak serum levels were seen 30 to 90 minutes after dosing. When healthy volunteers received equivalent doses of regular human insulin, peak insulin levels occurred between 50 to 120 minutes after dosing. Similar results were seen in patients with type 1 diabetes (see Figure 2).

Figure 2: Serum HUMALOG and Insulin Levels After Subcutaneous Injection of Regular Human Insulin or HUMALOG (0.2 unit/kg) Immediately Before a High Carbohydrate Meal in 10 Patients with Type 1 Diabetes.a

a Baseline insulin concentration was maintained by infusion of 0.2 mU/min/kg human insulin.

HUMALOG was absorbed at a consistently faster rate than regular human insulin in healthy male volunteers given 0.2 unit/kg at abdominal, deltoid, or femoral subcutaneous sites. After HUMALOG was administered in the abdomen, serum drug levels were higher and the duration of action was slightly shorter than after deltoid or thigh administration. Bioavailability of HUMALOG is similar to that of regular human insulin. The absolute bioavailability after subcutaneous injection ranges from 55% to 77% with doses between 0.1 to 0.2 unit/kg, inclusive.

Distribution — After subcutaneous administration, the volume of distribution for HUMALOG is identical to that of regular human insulin, with a range of 0.26 to 0.36 L/kg. When administered intravenously, the volume of distribution of HUMALOG (range of 0.26 to 0.36 L/kg) was similar to that of regular human insulin (range of 0.32 to 0.67 L/kg).

Metabolism — Human metabolism studies have not been conducted. However, animal studies indicate that the metabolism of HUMALOG is identical to that of regular human insulin.

Elimination — After subcutaneous administration of HUMALOG, the t1/2 is shorter than that of regular human insulin (1 versus 1.5 hours, respectively). When administered intravenously, HUMALOG and regular human insulin demonstrated similar dose-dependent elimination, with a t1/2 of 0.44 hours (26 min) and 0.34 hours (20 min), respectively (0.1 unit/kg dose) and 0.86 hours (52 min) and 1.1 hours (66 min), respectively (0.2 unit/kg dose).

Specific Populations

Age — The effect of age on the pharmacokinetics of HUMALOG has not been studied. However, in large clinical trials, sub-group analysis based on age did not indicate any difference in postprandial glucose parameters between HUMALOG and regular human insulin.

Gender — The effect of gender on the pharmacokinetics of HUMALOG has not been studied. However, in large clinical trials, sub-group analysis based on gender did not indicate any difference in postprandial glucose parameters between HUMALOG and regular human insulin.

Renal Impairment — Type 2 diabetic patients with varying degree of renal impairment showed no difference in pharmacokinetics of regular insulin and HUMALOG. However, the sensitivity of the patients to insulin did change, with an increased response to insulin as the renal function declined. Some studies with human insulin have shown increased circulating levels of insulin in patients with renal impairment. Careful glucose monitoring and dose adjustments of insulin, including HUMALOG, may be necessary in patients with renal dysfunction [see Warnings and Precautions (5.5)].

Hepatic Impairment — Type 2 diabetic patients with impaired hepatic function showed no effect on the pharmacokinetic of HUMALOG as compared to patients with no hepatic dysfunction. However, some studies with human insulin have shown increased circulating levels of insulin in patients with liver failure. Careful glucose monitoring and dose adjustments of insulin, including HUMALOG, may be necessary in patients with hepatic dysfunction.

Race – The effects of race on the pharmacokinetics and pharmacodynamics of HUMALOG have not been studied.

Obesity – The effect of obesity on the pharmacokinetics and pharmacodynamics of HUMALOG has not been studied.

Pregnancy – The effect of pregnancy on the pharmacokinetics and pharmacodynamics of HUMALOG has not been studied [see Use in Specific Populations (8.1)].

Smoking – The effect of smoking on the pharmacokinetics and pharmacodynamics of HUMALOG has not been studied.

13 NONCLINICAL TOXICOLOGY

13.1 Carcinogenesis, Mutagenesis, Impairment of Fertility

Standard 2-year carcinogenicity studies in animals have not been performed. In Fischer 344 rats, a 12-month repeat-dose toxicity study was conducted with insulin lispro at subcutaneous doses of 20 and 200 units/kg/day (approximately 3 and 32 times the human subcutaneous dose of 1 unit/kg/day, based on units/body surface area). Insulin lispro did not produce important target organ toxicity including mammary tumors at any dose.

Insulin lispro was not mutagenic in the following genetic toxicity assays: bacterial mutation, unscheduled DNA synthesis, mouse lymphoma, chromosomal aberration and micronucleus assays.

Male fertility was not compromised when male rats given subcutaneous insulin lispro injections of 5 and 20 units/kg/day (0.8 and 3 times the human subcutaneous dose of 1 unit/kg/day, based on units/body surface area) for 6 months were mated with untreated female rats. In a combined fertility, perinatal, and postnatal study in male and female rats given 1, 5, and 20 units/kg/day subcutaneously (0.16, 0.8, and 3 times the human subcutaneous dose of 1 unit/kg/day, based on units/body surface area), mating and fertility were not adversely affected in either gender at any dose.

13.2 Animal Toxicology and /or Pharmacology

In standard biological assays in fasted rabbits, 0.2 unit/kg of insulin lispro injected subcutaneously had the same glucose-lowering effect and had a more rapid onset of action as 0.2 unit/kg of regular human insulin.

14 CLINICAL STUDIES

The safety and efficacy of HUMALOG were studied in children, adolescent, and adult patients with type 1 diabetes (n=789) and adult patients with type 2 diabetes (n=722).

14.1 Type 1 Diabetes — Adults and Adolescents

A 12-month, randomized, parallel, open-label, active-controlled study was conducted in patients with type 1 diabetes to assess the safety and efficacy of HUMALOG (n=81) compared with Humulin® R [REGULAR insulin human injection, USP (rDNA origin)] (n=86). HUMALOG was administered by subcutaneous injection immediately prior to meals and Humulin R was administered 30 to 45 minutes before meals. Humulin® U [ULTRALENTE® human insulin (rDNA origin) extended zinc suspension] was administered once or twice daily as the basal insulin. There was a 2- to 4-week run-in period with Humulin R and Humulin U before randomization. Most patients were Caucasian (97%). Forty-seven percent of the patients were male. The mean age was 31 years (range 12 to 70 years). Glycemic control, the total daily doses of HUMALOG and Humulin R, and the incidence of severe hypoglycemia (as determined by the number of events that were not self-treated) were similar in the two treatment groups. There were no episodes of diabetic ketoacidosis in either treatment group.

Table 4: Type 1 Diabetes Mellitus – Adults and Adolescents
Treatment Duration Treatment in Combination with: | 12 months Humulin U
 | HUMALOG | Humulin R
N | 81 | 86
Baseline HbA1c (%)a | 8.2 ± 1.4 | 8.3 ± 1.7
Change from baseline HbA1c (%)a | -0.1 ± 0.9 | 0.1 ± 1.1
Treatment Difference in HbA1c Mean (95% confidence interval) | 0.4 (0.0, 0.8)
Baseline short-acting insulin dose (units/kg/day) | 0.3 ± 0.1 | 0.3 ± 0.1
End-of-Study short-acting insulin dose (units/kg/day) | 0.3 ± 0.1 | 0.3 ± 0.1
Change from baseline short-acting insulin dose (units/kg/day) | -0.0 ± 0.1 | 0.0 ±0.1
Baseline Body weight (kg) | 72 ± 12.7 | 71 ± 11.3
Weight change from baseline (kg) | 1.4 ± 3.6 | 1.0 ± 2.6
Patients with severe hypoglycemia (n, %)b | 14 (17%) | 18 (21%)
a Values are Mean ± SD
b Severe hypoglycemia refers to hypoglycemia for which patients were not able to self-treat.

14.2 Type 2 Diabetes – Adults

A 6-month randomized, crossover, open-label, active-controlled study was conducted in insulin-treated patients with type 2 diabetes (n=722) to assess the safety and efficacy of HUMALOG for 3 months followed by Humulin R for 3 months or the reverse sequence. HUMALOG was administered by subcutaneous injection immediately before meals and Humulin R was administered 30 to 45 minutes before meals. Humulin® N [NPH human insulin (rDNA origin) isophane suspension] or Humulin U was administered once or twice daily as the basal insulin. All patients participated in a 2- to 4-week run-in period with Humulin R and Humulin N or Humulin U. Most of the patients were Caucasian (88%), and the numbers of men and women in each group were approximately equal. The mean age was 58.6 years (range 23.8 to 85 years). The average body mass index (BMI) was 28.2 kg/m^2. During the study, the majority of patients used Humulin N (84%) compared with Humulin U (16%) as their basal insulin. The reductions from baseline in HbA1c and the incidence of severe hypoglycemia (as determined by the number of events that were not self-treated) were similar between the two treatments from the combined groups (see Table 5).

Table 5: Type 2 Diabetes Mellitus — Adults
 |  | End point
 | Baseline | HUMALOG + Basal | Humulin R + Basal
HbA1c (%)a | 8.9 ± 1.7 | 8.2 ± 1.3 | 8.2 ± 1.4
Change from baseline HbA1c (%)a | — | -0.7 ± 1.4 | -0.7 ± 1.3
Short-acting insulin dose (units/kg/day)a | 0.3 ±0.2 | 0.3 ± 0.2 | 0.3 ±0.2
Change from baseline short-acting insulin dose (units/kg/day)a | — | 0.0 ± 0.1 | 0.0 ± 0.1
Body weight (kg)a | 80 ± 15 | 81 ± 15 | 81 ±15
Weight change from baseline | — | 0.8 ± 2.7 | 0.9 ± 2.6
Patients with severe hypoglycemia (n, %)b | — | 15 (2%) | 16 (2%)
a Values are Mean ± SD
b Severe hypoglycemia refers to hypoglycemia for which patients were not able to self-treat.

14.3 Type 1 Diabetes – Pediatric and Adolescents

An 8-month, crossover study of adolescents with type 1 diabetes (n=463), aged 9 to 19 years, compared two subcutaneous multiple-dose treatment regimens: HUMALOG or Humulin R, both administered with Humulin N (NPH human insulin) as the basal insulin. HUMALOG achieved glycemic control comparable to Humulin R, as measured by HbA1c (see Table 6), and both treatment groups had a comparable incidence of hypoglycemia. In a 9-month, crossover study of prepubescent children (n=60) with type 1 diabetes, aged 3 to 11 years, HUMALOG administered immediately before meals, HUMALOG administered immediately after meals and Humulin R administered 30 minutes before meals resulted in similar glycemic control, as measured by HbA1c, and incidence of hypoglycemia, regardless of treatment group.

Table 6: Pediatric Subcutaneous Administration of HUMALOG in Type 1 Diabetes
 |  | End point
 | Baseline | HUMALOG + NPH | Humulin R + NPH
HbA1c (%)a | 8.6 ± 1.5 | 8.7 ± 1.5 | 8.7 ± 1.6
Change from baseline HbA1c (%)a | — | 0.1 ± 1.1 | 0.1 ± 1.3
Short-acting insulin dose (units/kg/day)a | 0.5 ± 0.2 | 0.5 ± 0.2 | 0.5 ± 0.2
Change from baseline short-acting insulin dose (units/kg/day)a | — | 0.01 ± 0.1 | -0.01 ± 0.1
Body weight (kg)a | 59.1 ± 13.1 | 61.1 ± 12.7 | 61.4 ± 12.9
Weight change from baseline (kg)a | — | 2.0 ± 3.1 | 2.3 ± 3.0
Patients with severe hypoglycemia (n, %)b | — | 5 (1.1%) | 5 (1.1%)
Diabetic ketoacidosis (n, %) | — | 11 (2.4%) | 9 (1.9%)
a Values are Mean ± SD
b Severe hypoglycemia refers to hypoglycemia that required glucagon or glucose injection or resulted in coma.

14.4 Type 1 Diabetes – Adults Continuous Subcutaneous Insulin Infusion

To evaluate the administration of HUMALOG via external insulin pumps, two open-label, crossover design studies were performed in patients with type 1 diabetes. One study involved 39 patients, ages 19 to 58 years, treated for 24 weeks with HUMALOG or regular human insulin. After 12 weeks of treatment, the mean HbA1c values decreased from 7.8% to 7.2% in the HUMALOG-treated patients and from 7.8% to 7.5% in the regular human insulin-treated patients. Another study involved 60 patients (mean age 39, range 15 to 58 years) treated for 24 weeks with either HUMALOG or buffered regular human insulin. After 12 weeks of treatment, the mean HbA1c values decreased from 7.7% to 7.4% in the HUMALOG-treated patients and remained unchanged from 7.7% in the buffered regular human insulin-treated patients. Rates of hypoglycemia were comparable between treatment groups in both studies.

14.5 Type 1 Diabetes – Pediatric Continuous Subcutaneous Insulin Infusion

A randomized, 16-week, open-label, parallel design, study of children and adolescents with type 1 diabetes (n=298) aged 4 to 18 years compared two subcutaneous infusion regimens administered via an external insulin pump: insulin aspart (n=198) or HUMALOG (n=100). These two treatments resulted in comparable changes from baseline in HbA1c and comparable rates of hypoglycemia after 16 weeks of treatment (see Table 7). Infusion site reactions were similar between groups.

Table 7: Pediatric Insulin Pump Study in Type 1 Diabetes (16 weeks; n=298)
 | HUMALOG | Aspart
N | 100 | 198
Baseline HbA1c (%)a | 8.2 ± 0.8 | 8.0 ± 0.9
Change from Baseline HbA1c (%) | -0.1 ± 0.7 | -0.1 ± 0.8
Treatment Difference in HbA1c, Mean (95% confidence interval) | 0.1 (-0.3, 0.1)
Baseline insulin dose (units/kg/24 hours)a | 0.9 ± 0.3 | 0.9 ± 0.3
End-of-Study insulin dose (units/kg/24 hours)a | 0.9 ± 0.2 | 0.9 ± 0.2
Patients with severe hypoglycemia (n, %)b | 8 (8%) | 19 (10%)
Diabetic ketoacidosis (n, %) | 0 (0) | 1 (0.5%)
Baseline body weight (kg)a | 55.5 ± 19.0 | 54.1 ± 19.7
Weight Change from baseline (kg)a | 1.6 ± 2.1 | 1.8 ± 2.1
a Values are Mean ± SD
b Severe hypoglycemia refers to hypoglycemia associated with central nervous system symptoms and requiring the intervention of another person or hospitalization.

16 HOW SUPPLIED/STORAGE AND HANDLING

16.1 How Supplied

HUMALOG 100 units per mL (U-100) is available as:

10 mL vials | NDC 0002-7510-01 (VL-7510)
3 mL vials | NDC 0002-7510-17 (VL-7533)
5 x 3 mL cartridges^1 | NDC 0002-7516-59 (VL-7516)
5 x 3 mL prefilled pen | NDC 0002-8725-59 (HP-8725)
5 x 3 mL Humalog KwikPen (prefilled) | NDC 0002-8799-59 (HP-8799)

16.2 Storage

Do not use after the expiration date.

Unopened HUMALOG should be stored in a refrigerator (36° to 46°F [2° to 8°C]), but not in the freezer. Do not use HUMALOG if it has been frozen. In-use HUMALOG vials, cartridges, pens, and HUMALOG KwikPen® should be stored at room temperature, below 86°F (30°C) and must be used within 28 days or be discarded, even if they still contain HUMALOG. Protect from direct heat and light. See table below:

 | Not In-Use (Unopened) Room Temperature (Below 86°F [30°C]) | Not In-Use (Unopened) Refrigerated | In-Use (Opened) Room Temperature, (Below 86°F [30°C])
10 mL vial | 28 days | Until expiration date | 28 days, refrigerated/room temperature.
3 mL vial | 28 days | Until expiration date | 28 days, refrigerated/room temperature.
3 mL cartridge | 28 days | Until expiration date | 28 days, Do not refrigerate.
3 mL prefilled pen | 28 days | Until expiration date | 28 days, Do not refrigerate.
3 mL Humalog KwikPen (prefilled) | 28 days | Until expiration date | 28 days, Do not refrigerate.

Use in an External Insulin Pump — Change the HUMALOG in the reservoir at least every 7 days, change the infusion sets and the infusion set insertion site at least every 3 days or after exposure to temperatures that exceed 98.6°F (37°C). A HUMALOG 3 mL cartridge used in the D-Tron pumps should be discarded after 7 days, even if it still contains HUMALOG. However, as with other external insulin pumps, the infusion set should be replaced and a new infusion set insertion site should be selected at least every 3 days.

Diluted HUMALOG for Subcutaneous Injection — Diluted HUMALOG may remain in patient use for 28 days when stored at 41°F (5°C) and for 14 days when stored at 86°F (30°C). Do not dilute HUMALOG contained in a cartridge or HUMALOG used in an external insulin pump.

16.3 Preparation and Handling

Diluted HUMALOG for Subcutaneous Injection — HUMALOG may be diluted with Sterile Diluent for HUMALOG for subcutaneous injection. Diluting one part HUMALOG to nine parts diluent will yield a concentration one-tenth that of HUMALOG (equivalent to U-10). Diluting one part HUMALOG to one part diluent will yield a concentration one-half that of HUMALOG (equivalent to U-50).

17 PATIENT COUNSELING INFORMATION

See FDA-approved patient labeling.

17.1 Instructions for All Patients

Patients should be instructed on self-management procedures including glucose monitoring, proper injection technique, and management of hypoglycemia and hyperglycemia. Patients must be instructed on handling of special situations such as intercurrent conditions (illness, stress, or emotional disturbances), an inadequate or skipped insulin dose, inadvertent administration of an increased insulin dose, inadequate food intake, and skipped meals. Refer patients to the HUMALOG Patient Information Leaflet for additional information.

Women with diabetes should be advised to inform their doctor if they are pregnant or are contemplating pregnancy.

Accidental mix-ups between HUMALOG and other insulins have been reported. To avoid medication errors between HUMALOG and other insulins, patients should be instructed to always check the insulin label before each injection.

17.2 For Patients Using Continuous Subcutaneous Insulin Pumps

Patients using external pump infusion therapy should be trained appropriately.

The following insulin pumps have been tested in HUMALOG clinical trials conducted by Eli Lilly and Company.

- Disetronic® H-Tron® plus V100, D-Tron® and D-Tronplus® with Disetronic Rapid infusion sets^2
- MiniMed® Models 506, 507 and 508 and Polyfin® infusion sets^3

HUMALOG is recommended for use in pump systems suitable for insulin infusion such as MiniMed, Disetronic, and other equivalent pumps. Before using HUMALOG in a pump system, read the pump label to make sure the pump is indicated for continuous delivery of fast-acting insulin. HUMALOG is recommended for use in any reservoir and infusion sets that are compatible with insulin and the specific pump. Please see recommended reservoir and infusion sets in the pump manual.

To avoid insulin degradation, infusion set occlusion, and loss of the preservative (metacresol), insulin in the reservoir should be replaced at least every 7 days; infusion sets and infusion set insertion sites should be changed at least every 3 days.

Insulin exposed to temperatures higher than 98.6°F (37°C) should be discarded. The temperature of the insulin may exceed ambient temperature when the pump housing, cover, tubing or sport case is exposed to sunlight or radiant heat. Infusion sites that are erythematous, pruritic, or thickened should be reported to the healthcare professional, and a new site selected because continued infusion may increase the skin reaction or alter the absorption of HUMALOG.

Pump or infusion set malfunctions or insulin degradation can lead to rapid hyperglycemia and ketosis. This is especially pertinent for rapid acting insulin analogs that are more rapidly absorbed through skin and have a shorter duration of action. Prompt identification and correction of the cause of hyperglycemia or ketosis is necessary. Problems include pump malfunction, infusion set occlusion, leakage, disconnection or kinking, and degraded insulin. Less commonly, hypoglycemia from pump malfunction may occur. If these problems cannot be promptly corrected, patients should resume therapy with subcutaneous insulin injection and contact their healthcare professionals. [See Dosage and Administration (2.3), Warnings and Precautions (5.7), and How Supplied/Storage and Handling (16)].

____________

^1 3 mL cartridge is for use in Eli Lilly and Company's HumaPen® Memoir™ and HumaPen® Luxura™ HD insulin delivery devices, Owen Mumford, Ltd.'s Autopen® 3-mL insulin delivery device and Disetronic D-TRON® and D-TRON® Plus pumps.

Autopen® is a registered trademark of Owen Mumford, Ltd.

Humalog®, Humalog® KwikPen™, HumaPen®, HumaPen® Memoir™, HumaPen® Luxura™ and HumaPen® Luxura™ HD are trademarks of Eli Lilly and Company.

^2 Disetronic®, H-Tron®, D-Tron®, and D-Tronplus® are registered trademarks of Roche Diagnostics GmbH.

^3 MiniMed® and Polyfin® are registered trademarks of MiniMed, Inc.

Other product and company names may be the trademarks of their respective owners.

Literature revised May 18, 2011
Marketed by: Lilly USA, LLC, Indianapolis, IN 46285, USA

www.humalog.com
Copyright © 1996, 2011, Eli Lilly and Company. All rights reserved.

PV 5533 AMP

Patient Information

HUMALOG®

insulin lispro injection, USP (rDNA origin)

Read the “Patient Information” that comes with HUMALOG (HU-ma-log) before you start using it and each time you get a refill. There may be new information. This leaflet does not take the place of talking with your healthcare provider about your diabetes or treatment. If you have questions about HUMALOG or diabetes, talk with your healthcare provider.

What is the most important information I should know about HUMALOG?

- Do not change the insulin you use without talking to your healthcare provider. Any change in insulin strength, manufacturer, type (regular, NPH, analog) may need a change in the dose you are using. This dose change may be needed right away or later on. Sometimes this dose change may happen during the first several weeks or months on the new insulin. Doses of oral anti-diabetic medicines may also need to change if your insulin is changed.
- You must test your blood sugar levels while using an insulin such as HUMALOG. Your healthcare provider will tell you how often you should test your blood sugar level, and what to do if it is high or low.
- When used in a pump do not mix HUMALOG with any other insulin or liquid.

What is HUMALOG?

HUMALOG (insulin lispro injection, USP [rDNA origin]) is an injectable rapid-acting man-made insulin. HUMALOG is used to treat people with diabetes for the control of high blood sugar.

- HUMALOG is a clear, colorless, sterile solution for injection under the skin (subcutaneously).
- You need a prescription to get HUMALOG. Always be sure you receive the right insulin from the pharmacy.

HUMALOG comes in:

- 10 mL vials (bottles) for use with a syringe or external insulin pump
- 3 mL vials (bottles) for use with a syringe or external insulin pump
- 3 mL prefilled pens
- 3 mL Humalog® KwikPen™
- 3 mL cartridges for use with a reusable pen or external insulin pump

Who should not take HUMALOG?

Do not take HUMALOG if:

- your blood sugar is too low (hypoglycemia). After treating your low blood sugar, follow your healthcare provider's instructions on the use of HUMALOG.
- you are allergic to insulin lispro or any of the ingredients in HUMALOG. See the end of this leaflet for a complete list of ingredients in HUMALOG. Check with your healthcare provider if you are not sure.

What should I tell my healthcare provider before taking HUMALOG?

Tell your healthcare provider:

- about all your medical conditions, including liver or kidney problems. Your dose may need to be adjusted.
- if you are pregnant or breastfeeding. You and your healthcare provider should talk about the best way to manage your diabetes while you are pregnant or breastfeeding. HUMALOG has not been studied in pregnant or nursing women.
- about all the medicines you take, including prescription and non-prescription medicines, vitamins and herbal supplements. Your HUMALOG dose may need to change if you take other medicines.

Know the medicines you take. Keep a list of your medicines with you to show your healthcare providers when you get a new medicine.

How should I use HUMALOG?

HUMALOG can be used with a syringe, prefilled pen, reusable pen or external insulin pump. Talk to your healthcare provider if you have any questions.

- Read the instructions for use that comes with your HUMALOG product. Talk to your healthcare provider if you have any questions. Your healthcare provider should show you how to inject HUMALOG before you start taking it.
- HUMALOG is a rapid-acting insulin. You should take HUMALOG within fifteen minutes before eating or right after eating a meal.
- Only use HUMALOG that is clear and colorless. If your HUMALOG is cloudy, colored, or has solid particles or clumps in it, return it to your pharmacy for a replacement.
- Do not mix HUMALOG:
  - with any type of insulin other than NPH when used with injections by syringe.
  - with any other insulin or liquid when used in a pump.
- If your doctor recommends diluting HUMALOG, follow your doctor's instructions exactly so that you know:
  - How to make HUMALOG more dilute (that is, a smaller number of units of HUMALOG for a given amount of liquid) and
  - How to use this more dilute form of HUMALOG. Do not use dilute insulin in a pump.
- Inject HUMALOG under your skin (subcutaneously) in your upper arm, abdomen (stomach area), thigh (upper leg), or buttocks. Never inject it into a vein or muscle.
- Change (rotate) your injection site with each dose.
- If you have type 1 diabetes, you need to take a longer-acting insulin in addition to HUMALOG (except when using an external insulin pump).
- If you have type 2 diabetes, you may be taking oral anti-diabetic medicines and/or a longer-acting insulin in addition to HUMALOG.
- Follow the instructions given by your healthcare provider about the type or types of insulin you are using. Do not make any changes with your insulin unless you have talked to your healthcare provider. Always make sure that you received the correct type of HUMALOG from the pharmacy. Check to make sure you are injecting the correct insulin and dose, especially if you use other insulin with HUMALOG.
- If you take too much HUMALOG, your blood sugar may fall low (hypoglycemia). You can treat mild low blood sugar by drinking or eating something sugary right away (fruit juice, sugar candies, or glucose tablets). It is important to treat low blood sugar right away because it could get worse and you could pass out (become unconscious). If you pass out, you will need help from another person or emergency medical services right away, and will need treatment with glucagon injection or treatment at a hospital. See “What are the possible side effects of HUMALOG?” for more information on low blood sugar.
- If you forget to take your dose of HUMALOG, your blood sugar may go too high (hyperglycemia). If high blood sugar is not treated it can lead to serious problems like loss of consciousness (passing out), coma or even death. Follow your healthcare provider's instructions for treating high blood sugar. Know your symptoms of high blood sugar which may include:
  - increased thirst
  - frequent urination
  - drowsiness
  - loss of appetite
  - a hard time breathing
  - fruity smell on the breath
  - high amounts of sugar and ketones in your urine
  - nausea, vomiting (throwing up) or stomach pain
- Your insulin dosage may need to change because of:
  - illness
  - stress
  - other medicines you take
  - change in diet
  - change in physical activity or exercise

What are the possible side effects of HUMALOG?

- low blood sugar (hypoglycemia). Symptoms of low blood sugar may include:
  - sweating
  - dizziness or lightheadedness
  - shakiness
  - hunger
  - fast heart beat
  - tingling of lips and tongue
  - trouble concentrating or confusion
  - blurred vision
  - slurred speech
  - anxiety, irritability or mood changes
  - headache
- Severe low blood sugar can cause unconsciousness (passing out), seizures, and death. Low blood sugar may affect your ability to drive a car or use mechanical equipment, risking injury to yourself or others. Know your symptoms of low blood sugar. Follow your healthcare provider's instructions for treating low blood sugar. Talk to your healthcare provider if low blood sugar is a problem for you.
- Serious allergic reaction (whole body reaction). Get medical help right away, if you develop a rash over your whole body, have trouble breathing, a fast heartbeat, or sweating.
- Reactions at the injection site (local allergic reaction). You may get redness, swelling, and itching at the injection site. If you keep having skin reactions or they are serious, talk to your healthcare provider. You may need to stop using HUMALOG and use a different insulin. Do not inject insulin to skin that is red, swollen or itchy.
- Skin thickens or pits at the injection site (lipodystrophy). Change (rotate) when you inject your insulin to help to prevent these skin changes from happening. Do not inject insulin into this type of skin.
- Swelling of your hands and feet
- Low potassium in your blood (hypokalemia)
- Weight gain

These are not all of the possible side effects from HUMALOG. Ask your healthcare provider or pharmacist for more information.

Call your doctor for medical advice about side effects. You may report side effects to FDA at 1-800-FDA-1088.

How should I store HUMALOG?

- Store all unopened (unused) HUMALOG in the original carton in a refrigerator at 36°F to 46°F (2°C to 8°C).
- Do not freeze. Do not use HUMALOG if it has been frozen.
- Keep unopened HUMALOG in the carton to protect from light.

After starting use (open)

Vials:

- Keep in the refrigerator or at room temperature below 86°F (30°C) for up to 28 days.
- Keep vials away from direct heat or light.
- Throw away an opened vial after 28 days of use, even if there is insulin left in the vial.
- Unopened vials can be used until the expiration date on the HUMALOG carton and label, if the medicine has been stored in a refrigerator.

Cartridge and Prefilled Pens:

- Keep at room temperature below 86°F (30°C) for up to 28 days.
- Do not store a cartridge or prefilled pen that you are using in the refrigerator.
- Keep cartridges and prefilled pens away from direct heat or light.
- A cartridge used in the D-Tron^1 or D-Tronplus^1 pump may be used for up to 7 days.
- Throw away a used cartridge or prefilled pen after 28 days, even if there is insulin left in the cartridge or the pen.

General Information about HUMALOG

- HUMALOG in the pump reservoir and the complete external pump infusion set:
  - When HUMALOG is used in pumps, use only pumps that are recommended by your healthcare provider.
  - The infusion set and infusion site should be changed at least every 3 days.
  - The insulin in the reservoir should be changed at least every 7 days even if you have not used all of the insulin.
  - Change the infusion set and infusion site more often than every 3 days if you have high blood sugar (hyperglycemia), the pump alarms sounds, or the insulin flow is blocked (occlusion).
- Do not use HUMALOG for a condition for which it was not prescribed. Do not give or share HUMALOG with another person, even if they also have diabetes. It may harm them.
- This leaflet summarizes the most important information about HUMALOG. If you would like more information, talk with your healthcare provider. You can ask your healthcare provider for information about HUMALOG that is written for healthcare providers. For more information about HUMALOG, call 1-800-LillyRx (1-800-545-5979) or visit www.humalog.com.

What are the ingredients in HUMALOG?

insulin lispro, glycerin, dibasic sodium phosphate, metacresol, zinc oxide (zinc ion), trace amounts of phenol and water for injection.

Helpful information for people with diabetes is published by the American Diabetes Association, 1660 Duke Street, Alexandria, VA 22314 and on www.diabetes.org.

__________

^1 D-Tron®, D-Tronplus® are registered trademarks of Roche Diagnostics GmbH.

Humalog® and Humalog® KwikPen™ are registered trademarks of Eli Lilly and Company.

Patient Information revised May 23, 2011

Marketed by: Lilly USA, LLC, Indianapolis, IN 46285, USA

www.humalog.com

Copyright © 2007, 2011, Eli Lilly and Company. All rights reserved.

PV 5564 AMP

PATIENT INFORMATION

Humalog® KwikPen™
insulin lispro injection, USP (rDNA origin)

Disposable Insulin Delivery Device
User Manual

________________________________________________________________________________________

Introduction

Humalog® KwikPen™ (“Pen”) is designed for ease of use. It is a disposable insulin delivery device (“insulin Pen”) containing 3 mL (300 units) of U-100 Humalog® [insulin lispro injection, USP (rDNA origin)] insulin. You can inject from 1 to 60 units of Humalog in one injection. You can dial your dose one unit at a time. If you dial too many units, you can dial backwards to correct the dose without wasting any insulin.

Before using Humalog KwikPen, read the entire manual completely and follow the directions carefully. If you do not follow these directions completely, you may get too much or too little insulin.
Do not share your Humalog KwikPen or needles with anyone else. You may give an infection to them or get an infection from them.
DO NOT USE your KwikPen if any part appears broken or damaged. Contact Lilly at 1-800-Lilly-Rx (1-800-545-5979) or your healthcare professional for a replacement Pen. Always carry an extra Pen in case yours is lost or damaged.
This Pen is not recommended for use by the blind or visually impaired persons without the assistance of a person trained in the proper use of the product.

Preparing Humalog KwikPen

Important Notes

- Read and follow the directions provided in the Patient Information Leaflet.
- Check the label on your Pen before each injection for the expiration date and to make sure you are using the correct type of insulin.
- Your healthcare professional has prescribed the best type of insulin for you. Any changes in insulin therapy should be made only under medical supervision.
- KwikPen is recommended for use with Becton, Dickinson and Company pen needles.
- Be sure the needle is completely attached to the Pen before use.
- Do not share your Pen or needles.
- Keep these directions for future reference.

Frequently Asked Questions about Preparing Humalog KwikPen

- What should my insulin look like? Humalog is clear and colorless. If your Humalog is cloudy, colored, or has solid particles or clumps in it, return it to your pharmacy for a replacement. Be sure to refer to your Patient Information Leaflet for the appearance of your specific insulin.
- Why should I use a new needle for each injection? This will help ensure sterility. If needles are reused, you may get the wrong amount of insulin, a clogged needle or a jammed Pen.
- What should I do if I am not sure how much insulin remains in my cartridge? Hold the Pen with the needle end pointing down. The scale on the clear Cartridge Holder shows an estimate of the number of units remaining. These numbers should NOT be used for measuring an insulin dose.

Priming Humalog KwikPen

Important Notes

- Prime every time. The Pen must be primed to a stream of insulin before each injection to make sure the Pen is ready to dose.
- If you do not prime, you may get too much or too little insulin.

Frequently Asked Questions about Priming

- Why should I prime my KwikPen before each dose?
  1. Ensures that the Pen is ready to dose.
  2. Confirms that a stream of insulin comes out of the tip of the needle when you push the Dose Knob in.
  3. Removes air that may collect in the needle or insulin cartridge during normal use.
- What should I do if I cannot completely push in the Dose Knob when priming the KwikPen?
  1. Attach a new needle.
  2. Prime the Pen.
- What should I do if I see an air bubble in the cartridge? You need to prime the Pen. Remember, do not store the Pen with the needle attached as this may cause air bubbles to collect in the insulin cartridge. A small air bubble will not affect your dose and you can continue to take your dose as usual.

Injecting Your Dose

Important Notes

- Follow the instructions for sanitary injection technique recommended by your healthcare professional.
- Make sure you receive your complete dose by pushing and holding the dose knob in and count to 5 slowly before removing the needle. If insulin is leaking from the Pen you may not have held it in your skin long enough.
- The Pen will not allow you to dial more than the number of units left in the Pen.
- If your dose is greater than the number of units left in the Pen, you may either inject the amount remaining in your current Pen and then use a new Pen to complete your dose OR inject the full dose with a new Pen.
- Do not attempt to inject your insulin by turning the Dose Knob. You will NOT receive your insulin by turning the Dose Knob. You must PUSH the Dose Knob straight in for the dose to be delivered.
- Do not attempt to change the dose while injecting.
- The directions regarding needle handling are not intended to replace local, healthcare professional or institutional policies.
- Remove the needle after completing each injection.

Frequently Asked Questions about Injecting Your Dose

- Why is it difficult to push the Dose Knob when I try to inject?
  1. Your needle may be clogged. Try attaching a new needle. When you do this you may see insulin come out of the needle. Then prime the Pen.
  2. Pressing the Dose Knob quickly may make the Dose Knob harder to push. Pressing the Dose Knob more slowly may make it easier.
  3. Using a larger diameter needle will make it easier to push the Dose Knob during your injection. See your healthcare professional to determine which needle size is best for you.
  4. If the Dose Knob continues to be difficult to push after following the steps above, try the steps below under “What should I do if my KwikPen is jammed?”.
- What should I do if my KwikPen is jammed? Your Pen may be jammed if it is difficult to inject a dose or dial a dose. To clear the jam:
  1. Attach a new needle. When you do this you may see insulin come out of the needle.
  2. Prime the Pen.
  3. Dial your dose and inject.
  4. If the Dose Knob is still difficult to push, contact Lilly at 1-800-Lilly-Rx
    (1-800-545-5979).
- Why is insulin leaking from the needle after I finished injecting my dose? You may have removed the needle from your skin too quickly.
  1. Make sure you see a 0 in the Dose Window to confirm you received the complete dose.
  2. For the next dose, push and hold the Dose Knob in and count to 5 slowly before removing the needle.
- What should I do if my dose is dialed and the Dose Knob is accidentally pushed in without a needle attached?
  1. Dial back to zero.
  2. Attach a new needle. When you do this you may see insulin come out of the needle.
  3. Prime the Pen.
  4. Dial your dose and inject.
- What should I do if I dial a wrong dose (too high or too low)? Turn the Dose Knob backward or forward to correct the dose before injecting.
- What should I do if I see insulin leaking from the KwikPen needle while dialing the dose or correcting the dose? Do not inject the dose because you may not get your complete dose. Dial the Pen down to zero and prime the Pen again (see “Priming Humalog KwikPen” steps 2 B-D). Dial your dose and inject.
- What should I do if my full dose cannot be dialed? The Pen will not allow you to dial a dose greater than the number of insulin units remaining in the cartridge. For example, if you need 31 units and only 25 units remain in the cartridge you will not be able to dial past 25. Do not attempt to dial past this point. You may either:
  1. Inject the partial dose and then inject the remaining dose using a new Pen.
    or
  2. Inject the full dose with a new Pen.
- Why can I not dial the dose to use the small amount of insulin that remains in my cartridge? The Pen is designed to deliver at least 300 units of insulin. The Pen design prevents the cartridge from being completely emptied because the small amount of insulin that remains in the cartridge cannot be delivered.

Storage and Disposal

Important Notes

- Refer to the Patient Information Leaflet for complete insulin storage instructions.
- Pens that have not been used should be stored in a refrigerator but not in a freezer. Do not use a Pen if it has been frozen.
- Do not store the Pen with the needle attached. If the needle remains attached, insulin may leak from the Pen, insulin may dry inside the needle causing the needle to clog, or air bubbles may form inside the cartridge.
- The Pen you are currently using should be kept at room temperature and away from heat and light.
- Keep the Pen out of the reach of children.
- Dispose of used needles in a puncture-resistant container or as directed by your healthcare professional.
- Dispose of used Pens as instructed by your healthcare professional and without the needle attached.

Use the space below to keep track of how long you should use each Pen in the carton. Once you start using a KwikPen it must be thrown out after the number of days listed in your Patient Information Leaflet, even if there is insulin remaining in the Pen. Record the date you start using a Pen, find the number of days that KwikPen should be used in the Patient Information Leaflet and determine the date the Pen should be thrown out. Record the dates in the space provided below.

Example:

Pen 1 - First used on _______ + | Number of days you should = | Throw out on ______
Date | use KwikPen (from Patient | Date
 | Information Leaflet)
Pen 1 - First used on _______ | Throw out on _______
Date | Date
Pen 2 - First used on _______ | Throw out on _______
Date | Date
Pen 3 - First used on _______ | Throw out on _______
Date | Date
Pen 4 - First used on _______ | Throw out on _______
Date | Date
Pen 5 - First used on _______ | Throw out on _______
Date | Date

If you have any questions or problems with your Humalog KwikPen, contact Lilly at 1-800-Lilly-Rx (1-800-545-5979) or your healthcare professional for assistance.

For more information on Humalog KwikPen and insulin, please visit our website at www.humalog.com

Humalog® and Humalog® KwikPen™ are trademarks of Eli Lilly and Company.

Marketed by: Lilly USA, LLC
Indianapolis, IN 46285, USA

Copyright © 2007, 2011, Eli Lilly and Company. All rights reserved.

Humalog KwikPen meets the current dose accuracy and functional requirements of ISO 11608-1:2000.

Getting Ready
Make sure you have the following items: | □ Humalog® KwikPen™ | □ New Pen Needle | □ Alcohol Swab

Pen Parts | KwikPen, and Needle* Assembly *sold separately

Follow these instructions for each injection
1. Preparing Humalog KwikPen
A. | B. |  | C.
Pull Pen Cap to remove. Be sure to check your insulin for:; - Type - Expiration date - Appearance; Use an alcohol swab to wipe the Rubber Seal on the end of the Cartridge Holder. | Remove Paper Tab from Outer Needle Shield. |  | Push capped needle straight onto the Pen. Screw needle on until secure.

2. Priming Humalog KwikPen
Caution: If you do not prime before each injection, you may get too much or too little insulin.
A. | B. | C. | D.
Pull off Outer Needle Shield. Do not throw away. Pull off Inner Needle Shield and throw away. | Dial 2 Units by turning the Dose Knob. | Point Pen up. Tap Cartridge Holder to collect air at top. |  | With needle pointing up, push Dose Knob in until it stops and 0 is seen in the Dose Window.
Pull off Outer Needle Shield. Do not throw away. Pull off Inner Needle Shield and throw away. | Dial 2 Units by turning the Dose Knob. | Point Pen up. Tap Cartridge Holder to collect air at top. | Hold Dose Knob in and count to 5 slowly. Priming is complete when a stream of insulin appears from the needle tip and you have counted to 5 slowly. If a stream of insulin does not appear, repeat priming steps 2 B-D up to four times. If the Pen still does not prime, change the needle and repeat the priming steps above. Note: If you do not see a stream of insulin from the tip of the needle and the Dose Knob becomes hard to push, then change the needle and prime the Pen.

3. Injecting Your Dose
A. | B. |  | C. | D.
Turn Dose Knob to the number of units you need to inject. If you dial too many units, you can correct the dose by dialing backwards. Example: 10 units shown. Example: 15 units shown. The even numbers are printed on the dial. The odd numbers, after the number one, are shown as full lines. | Insert needle into skin using injection technique recommended by your healthcare professional. Place your thumb on the Dose Knob and push firmly until the Dose Knob stops. Note: The Pen will not allow you to dial more than the number of units left in the Pen. | To deliver the full dose, hold Dose Knob in and count to 5 slowly. Remove needle from skin. Note: Check to make sure you see 0 in the Dose Window to confirm you received the complete dose. | Carefully replace the Outer Needle Shield. Note: Remove the needle after each injection to keep air out of the cartridge. Do not store the Pen with the needle attached. | Unscrew the capped needle and dispose of as directed by your healthcare professional. Replace Pen Cap.

Literature revised October 28, 2011

PV 5592 AMP

PACKAGE LABEL

NDC 55045-3602-01

10 mL

100 units per mL

Humalog®

insulin lispro injection, USP

(rDNA origin)

For subcutaneous use.

Rx only